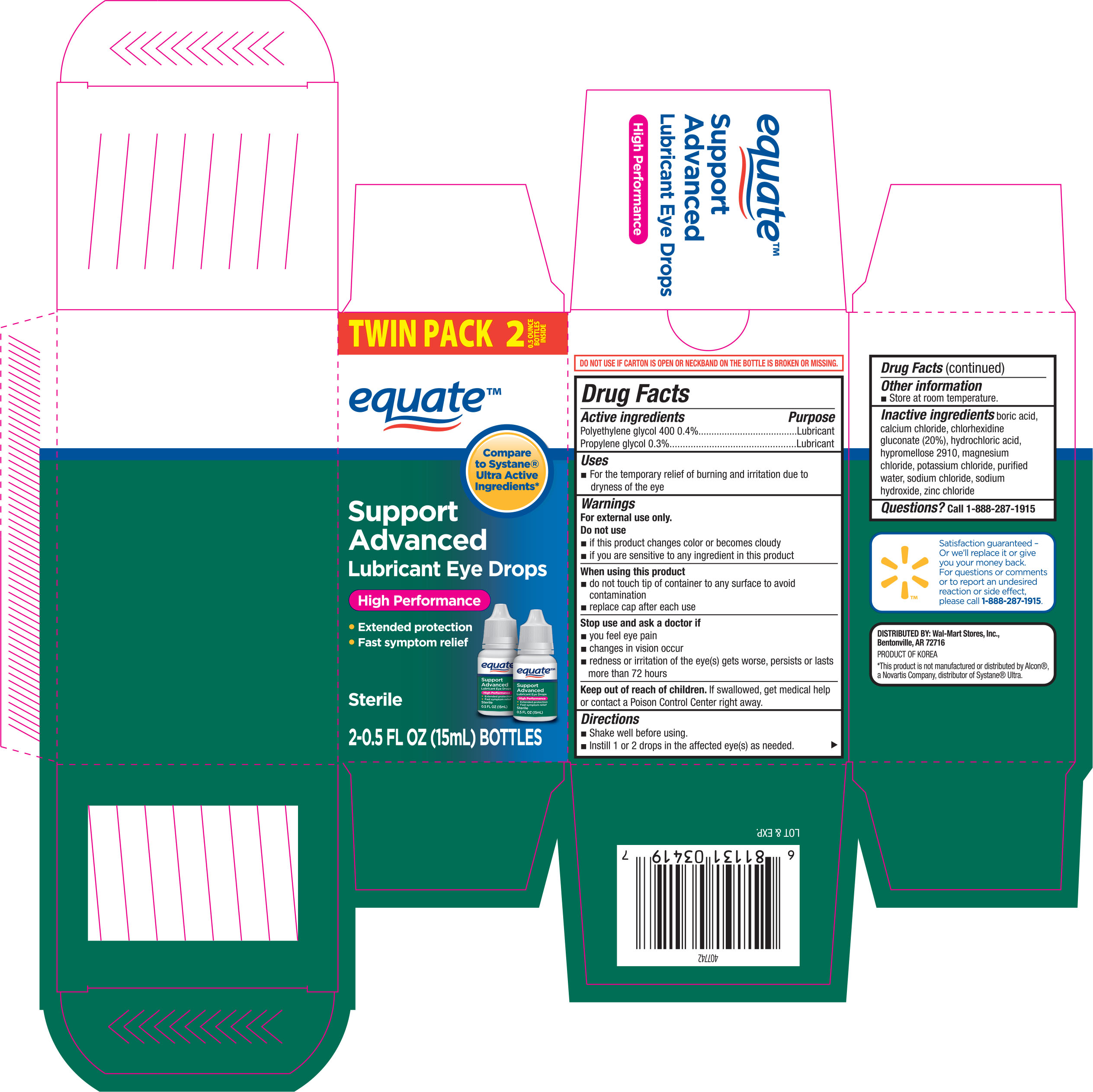 DRUG LABEL: Equate Support Advanced Lubricant
NDC: 49035-419 | Form: SOLUTION/ DROPS
Manufacturer: Wal-mart Stores Inc
Category: otc | Type: HUMAN OTC DRUG LABEL
Date: 20160309

ACTIVE INGREDIENTS: POLYETHYLENE GLYCOL 400 4 mg/1 mL; propylene glycol 3 mg/1 mL
INACTIVE INGREDIENTS: BORIC ACID; CALCIUM CHLORIDE; CHLORHEXIDINE GLUCONATE; HYDROCHLORIC ACID; HYPROMELLOSE 2910 (15 MPA.S); MAGNESIUM CHLORIDE; POTASSIUM CHLORIDE; WATER; SODIUM CHLORIDE; SODIUM HYDROXIDE; ZINC CHLORIDE

Active ingredients Purpose

Polyethylene glycol 400 0.4%...........................................Lubricant

Propylene glycol 0.3%.....................................................Lubricant

Uses

- For the temporary relief of burning and irritation due to dryness of the eye

Warnings

For external use only.

Do not use

- if this product changes color or becomes cloudy
- if you are sensitive to any ingredient in this product

When using this product

- do not touch tip of container to any surface to avoid contamination
- replace cap after each use

Stop use and ask a doctor if

- you feel eye pain
- changes in vision occur
- redness or irritation of the eye(s) gets worse, persists or lasts more than 72 hours

Keep out of reach of children. If swallowed, get medical help or contact a Poison Control Center right away.

Directions

- Shake well before using.
- Instill 1 or 2 drops in the affected eye(s) as needed.

Other information

- Store at room temperature.

Inactive ingredients

boric acid, calcium chloride, chlorhexidine gluconate (20%), hydrochloric acid, hypromellose 2910, magnesium chloride, potassium chloride, purified water, sodium chloride, sodium hydroxide, zinc chloride

DOSAGE AND ADMINISTRATION

Distributed by:

Wal-Mart Stores, Inc.

Bentonville, AR 72716

Product of Korea